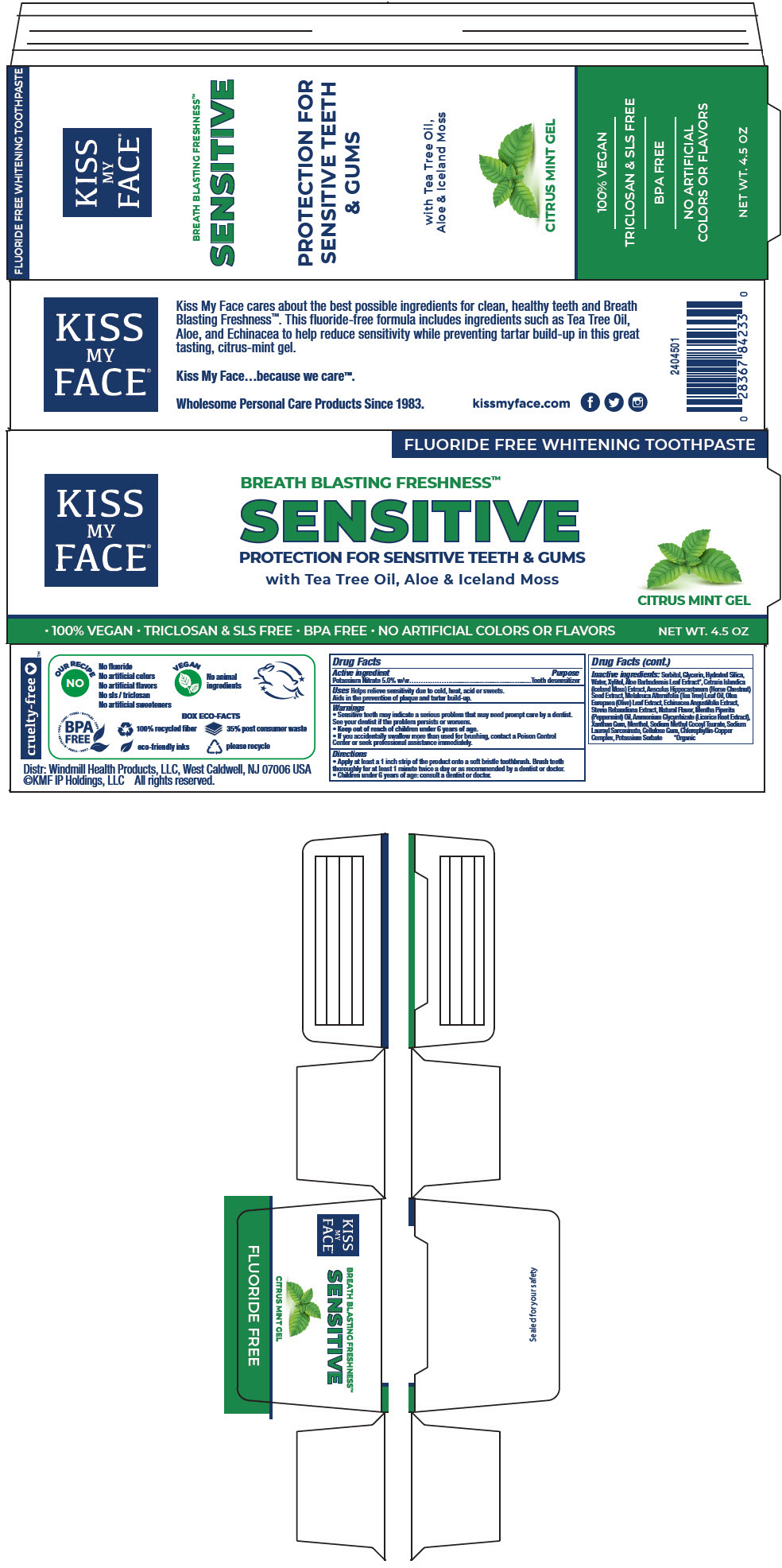 DRUG LABEL: Kiss My Face Sensitive Fluoride-Free Whitening - Citrus Mint
NDC: 74154-015 | Form: PASTE, DENTIFRICE
Manufacturer: Windmill Health Products, LLC
Category: otc | Type: HUMAN OTC DRUG LABEL
Date: 20220208

ACTIVE INGREDIENTS: Potassium Nitrate 0.05 g/1 g
INACTIVE INGREDIENTS: Sorbitol; Glycerin; Hydrated Silica; Water; Xylitol; Aloe Vera Leaf; CETRARIA ISLANDICA WHOLE; HORSE CHESTNUT; Tea Tree Oil; OLEA EUROPAEA LEAF; Echinacea Angustifolia Whole; STEVIA REBAUDIUNA LEAF; PEPPERMINT OIL; Licorice; Xanthan Gum; MENTHOL, UNSPECIFIED FORM; Sodium Methyl Cocoyl Taurate; Sodium Lauroyl Sarcosinate; CARBOXYMETHYLCELLULOSE SODIUM, UNSPECIFIED; SODIUM COPPER CHLOROPHYLLIN; Potassium Sorbate

Kiss My Face® Sensitive Fluoride-Free Whitening Toothpaste - Citrus Mint

Drug Facts

Active ingredient

Potassium Nitrate 5.0% w/w

Purpose

Tooth desensitizer

Uses

Helps relieve sensitivity due to cold, heat, acid or sweets.

Aids in the prevention of plaque and tartar build-up.

Warnings

- Sensitive teeth may indicate a serious problem that may need prompt care by a dentist. See your dentist if the problem persists or worsens.

- Keep out of reach of children under 6 years of age.
- If you accidentally swallow more than used for brushing, contact a Poison Control Center or seek professional assistance immediately.

Directions

- Apply at least a 1 inch strip of the product onto a soft bristle toothbrush. Brush teeth thoroughly for at least 1 minute twice a day or as recommended by a dentist or doctor.
- Children under 6 years of age: consult a dentist or doctor.

Inactive ingredients

Sorbitol, Glycerin, Hydrated Silica, Water, Xylitol, Aloe Barbadensis Leaf Extract [Organic] , Cetraria Islandica (Iceland Moss) Extract, Aesculus Hippocastanum (Horse Chestnut) Seed Extract, Melaleuca Alternifolia (Tea Tree) Leaf Oil, Olea Europaea (Olive) Leaf Extract, Echinacea Angustifolia Extract, Stevia Rebaudiana Extract, Natural Flavor, Mentha Piperita (Peppermint) Oil, Ammonium Glycyrrhizate (Licorice Root Extract), Xanthan Gum, Menthol, Sodium Methyl Cocoyl Taurate, Sodium Lauroyl Sarcosinate, Cellulose Gum, Chlorophyllin-Copper Complex, Potassium Sorbate

PRINCIPAL DISPLAY PANEL - 127 g Tube Carton

FLUORIDE FREE WHITENING TOOTHPASTE

KISS
MY
FACE®

BREATH BLASTING FRESHNESS™
SENSITIVE

PROTECTION FOR SENSITIVE TEETH & GUMS
with Tea Tree Oil, Aloe & Iceland Moss

CITRUS MINT GEL

• 100% VEGAN • TRICLOSAN & SLS FREE • BPA FREE • NO ARTIFICIAL COLORS OR FLAVORS
NET WT. 4.5 OZ